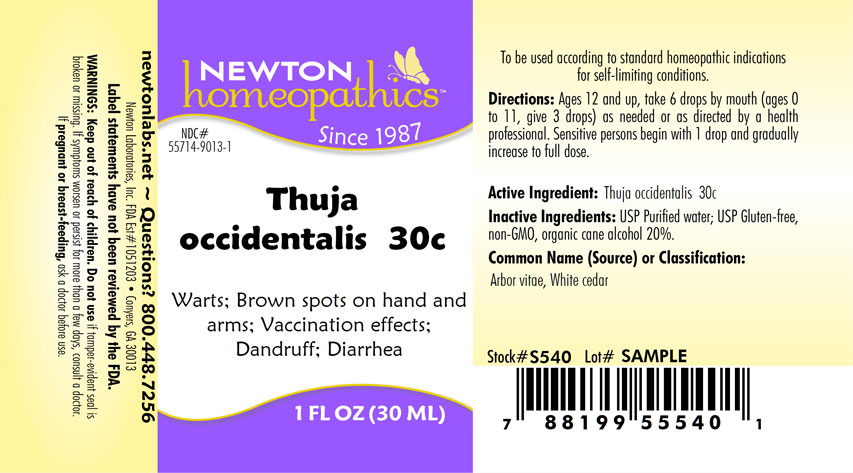 DRUG LABEL: Thuja occidentalis
NDC: 55714-9013 | Form: LIQUID
Manufacturer: Newton Laboratories, Inc.
Category: homeopathic | Type: HUMAN OTC DRUG LABEL
Date: 20250210

ACTIVE INGREDIENTS: THUJA OCCIDENTALIS LEAFY TWIG 30 [hp_C]/1 mL
INACTIVE INGREDIENTS: ALCOHOL; WATER

Thuja 9013L

INDICATIONS & USAGE SECTION

Warts; Brown spots on hand and arms; Vaccination effects; Dandruff; Diarrhea

DOSAGE & ADMINISTRATION SECTION

Directions: Ages 12 and up, take 6 drops by mouth, (ages 0 to 11, give 3 drops) as needed or as directed by a health professional. Sensitive persons begin with 1 drop and gradually increase to full dose.

OTC - ACTIVE INGREDIENT SECTION

Thuja occidentalis 30c

OTC - PURPOSE SECTION

Warts; Brown spots on hand and arms; Vaccination effects; Dandruff; Diarrhea

INACTIVE INGREDIENT SECTION

Inactive Ingredients: USP Purified Water; USP Gluten-free, non-GMO, organic cane alcohol 20%.

QUESTIONS SECTION

newtonlabs.net – Questions? 800.448.7256

Newton Laboratories, Inc. FDA Est # 1051203 - Conyers, GA 30013

WARNINGS SECTION

Warning: Keep out of reach of children. Do not use if tamper - evident seal is broken or missing. If symptoms worsen or persist for more than a few days, consult a doctor. If pregnant or breast-feeding, ask a doctor before use.

OTC - PREGNANCY OR BREAST FEEDING SECTION

If pregnant or breast-feeding, ask a doctor before use.

OTC - KEEP OUT OF REACH OF CHILDREN SECTION

Keep out of reach of children.